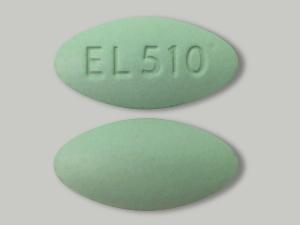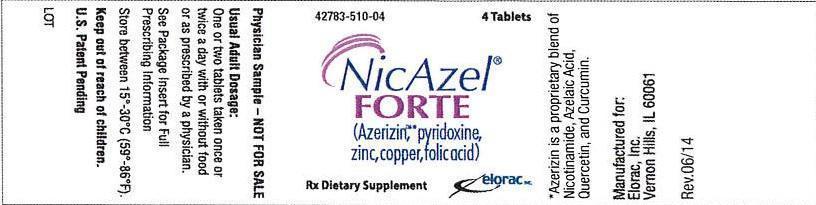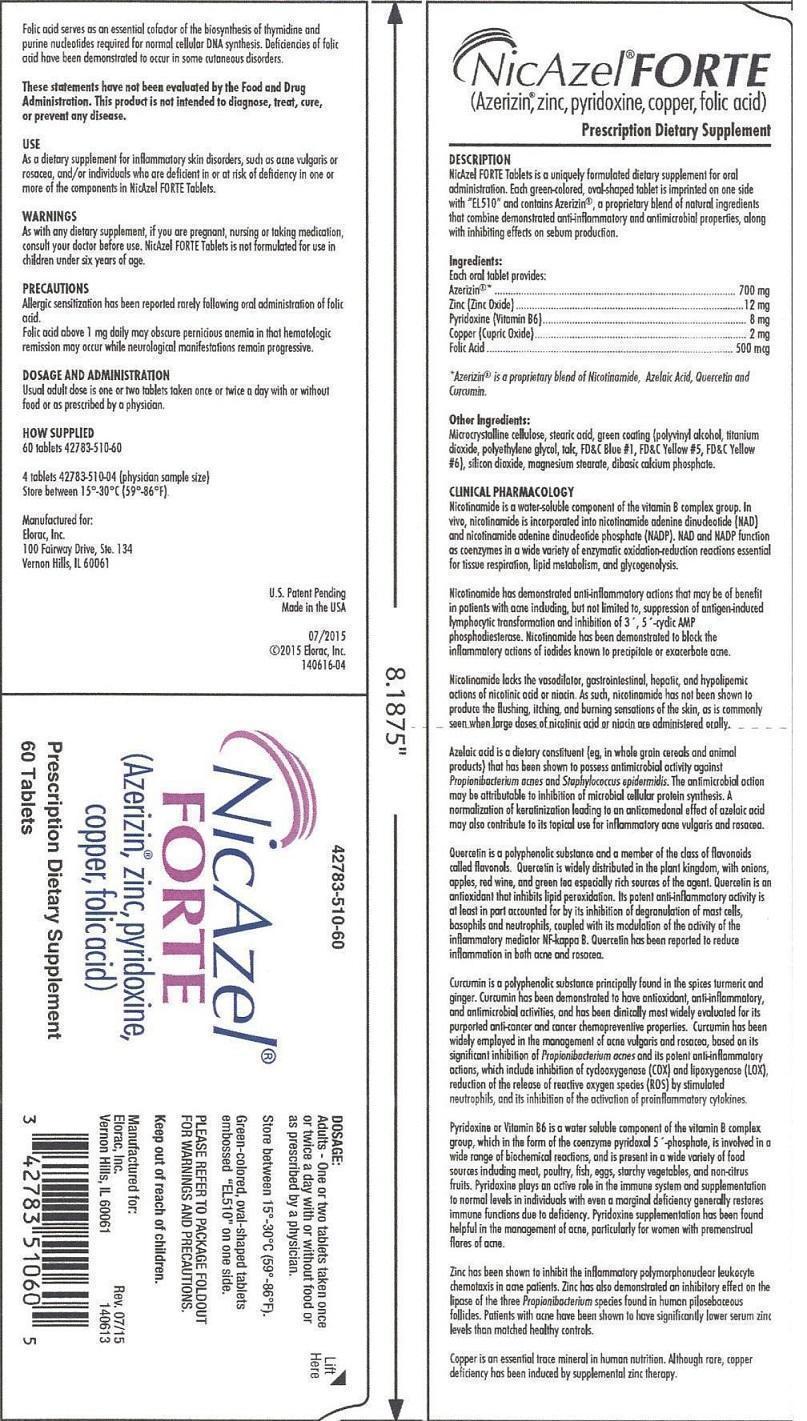 DRUG LABEL: NicAzelFORTE
NDC: 42783-510 | Form: TABLET
Manufacturer: Elorac, Inc
Category: other | Type: DIETARY SUPPLEMENT
Date: 20211208

ACTIVE INGREDIENTS: ZINC OXIDE 12 mg/1 1; PYRIDOXINE 8 mg/1 1; CUPRIC OXIDE 2 mg/1 1; FOLIC ACID 500 ug/1 1
INACTIVE INGREDIENTS: STEARIC ACID; POLYVINYL ALCOHOL; TITANIUM DIOXIDE; POLYETHYLENE GLYCOL, UNSPECIFIED; TALC; FD&C BLUE NO. 1; FD&C YELLOW NO. 5; FD&C YELLOW NO. 6; SILICON DIOXIDE; MAGNESIUM STEARATE; DIBASIC CALCIUM PHOSPHATE DIHYDRATE

NicAzel®FORTE
(Azerizin®, zinc, pyridoxine, copper, folic acid)
Prescription Dietary Supplement

NicAzel FORTE (Azerizin, zinc, pyridoxine, copper, folic acid)

Rx Dietary Supplement

DESCRIPTION

NicAzel FORTE Tablets is a uniquely formulated dietary supplement for oral administration. Each green-colored, oval-shaped tablet is imprinted on one side with “EL510” and contains Azerizin®, a proprietary blend of natural ingredients which combine demonstrated anti-inflammatory and anti-microbial properties, along with inhibiting effects on sebum production.

Ingredients:

Each tablet provides:

Azerizin®…………………………………….700 mg
Zinc (Zinc Oxide)……………………………..12 mg
Pyridoxine (Vitamin B6)……………………….8 mg
Copper (Cupric Oxide)…………………………2 mg
Folic Acid…………………………………...500 mcg

®Azerizin is a proprietary blend of Nicotinamide, Azelaic Acid, Quercetin and Curcumin.

Other Ingredients:

Microcrystalline cellulose, stearic acid, green coating (polyvinyl alcohol, titanium dioxide, polyethylene glycol, talc, FD&C Blue #1, FD&C Yellow #5, FD&C Yellow #6), silicon dioxide, magnesium stearate, dibasic calcium phosphate

CLINICAL PHARMACOLOGY

Nicotinamide is a water-soluble component of the vitamin B complex group. In vivo, nicotinamide is incorporated into nicotinamide adenine dinucleotide (NAD) and nicotinamide adenine dinucleotide phosphate (NADP). NAD and NADP function as coenzymes in a wide variety of enzymatic oxidation-reduction reactions essential for tissue respiration, lipid metabolism, and glycogenolysis.

Nicotinamide has demonstrated anti-inflammatory actions that may be of benefit in patients with acne including, but not limited to, suppression of antigen-induced lymphocytic transformation and inhibition of 3´, 5´-cyclic AMP phosphodiesterase. Nicotinamide has been demonstrated to block the inflammatory actions of iodides known to precipitate or exacerbate acne.

Nicotinamide lacks the vasodilator, gastrointestinal, hepatic, and hypolipemic actions of nicotinic acid or niacin. As such, nicotinamide has not been shown to produce the flushing, itching, and burning sensations of the skin, as is commonly seen when large doses of nicotinic acid or niacin are administered orally.

Azelaic acid is a dietary constituent (e.g., in whole grain cereals and animal products) that has been shown to possess antimicrobial activity against Propionibacterium acnes and Staphylococcus epidermidis. The antimicrobial action may be attributable to inhibition of microbial cellular protein synthesis. A normalization of keratinization leading to an anticomedonal effect of azelaic acid may also contribute to its topical use for inflammatory acne vulgaris and rosacea.

Quercetin is a polyphenolic substance and a member of the class of flavonoids called flavonols. Quercetin is widely distributed in the plant kingdom, with onions, apples, red wine and green tea especially rich sources of the agent. Quercetin is an antioxidant which inhibits lipid peroxidation. Its potent anti-inflammatory activity is at least in part accounted for by its inhibition of degranulation of mast cells, basophils and neutrophils, coupled with its modulation of the activity of the inflammatory mediator NF-kappa B. Quercetin has been reported to reduce inflammation in both acne and rosacea.

Curcumin is a polyphenolic substance principally found in the spices turmeric and ginger. Curcumin has been demonstrated to have antioxidant, anti-inflammatory, and antimicrobial activities, and has been clinically most widely evaluated for its purported anti-cancer and cancer chemopreventive properties. Curcumin has been widely employed in the management of acne vulgaris and rosacea, based on its significant inhibition of Propionibacterium acnes and its potent anti-inflammatory actions, which include inhibition of cyclooxygenase (COX) and lipoxygenase (LOX), reduction of the release of reactive oxygen species (ROS) by stimulated neutrophils, and its inhibition of the activation of proinflammatory cytokines.

Pyridoxine or Vitamin B6 is a water soluble component of the vitamin B complex group, which in the form of the coenzyme pyridoxal 5´-phosphate is involved in a wide range of biochemical reactions, and is present in a wide variety of food sources including meat, poultry, fish, eggs, starchy vegetables, and non-citrus fruits. Pyridoxine plays an active role in the immune system, and supplementation to normal levels in individuals with even a marginal deficiency generally restores immune functions due to deficiency. Pyridoxine supplementation has been found helpful in the management of acne, particularly for women with premenstrual flares of acne.

Zinc has been shown to inhibit the inflammatory polymorphonuclear leukocyte chemotaxis in acne patients. Zinc has also demonstrated an inhibitory effect on the lipase of the three Propionibacterium species found in human pilosebaceous follicles. Patients with acne have been shown to have significantly lower serum zinc levels than matched healthy controls.

Copper is an essential trace mineral in human nutrition. Although rare, copper deficiency has been induced by supplemental zinc therapy.

Folic acid serves as an essential cofactor of the biosynthesis of thymidine and purine nucleotides required for normal cellular DNA synthesis. Deficiencies of folic acid have been demonstrated to occur in some cutaneous disorders.

These statements have not been evaluated by the Food and Drug Administration. This product is not intended to diagnose, treat, cure, or prevent any disease.

USE

As a dietary supplement for inflammatory skin disorders, such as acne vulgaris or rosacea, and/or individuals who are deficient in or at risk of deficiency in one or more of the components in NicAzel FORTE Tablets.

WARNINGS

As with any dietary supplement, if you are pregnant, nursing or taking medication, consult your doctor before use. NicAzel FORTE Tablets are not formulated for use in children under 6 years of age.

PRECAUTIONS

Allergic sensitization has been reported rarely following oral administration of folic acid.

Folic acid above 1 mg daily may obscure pernicious anemia in that hematologic remission may occur while neurological manifestations remain progressive.

DOSAGE & ADMINISTRATION

Usual adult dose is one or two tablets taken once or twice a day with or without food or as prescribed by a physician.

HOW SUPPLIED

60 tablets 42783-510-60

4 tablets 42783-510-04 (physician sample size)

Store between 15°-30°C (59°-86°F).

DOSAGE AND ADMINISTRATION

Manufactured for Elorac, Inc.
100 Fairway Drive, Ste. 134
Vernon Hills, IL 60061

U.S. Patent Pending

Made in the USA

07/2015

©2015 Elorac, Inc.
140616-04

Principal Display Panel with Package Insert (Booklet Label):

42783-510-04

NicAzel®FORTE
(Azerizin®, zinc, pyridoxine, copper, folic acid)

Prescription Dietary Supplement
4 Tablets

42783-510-60

NicAzel®FORTE
(Azerizin®, zinc, pyridoxine, copper, folic acid)

Prescription Dietary Supplement
60 Tablets

DOSAGE:

Adults: One or two tablets taken once or twice a day with or without food or as prescribed by a physician.

Store between 15 - 30 C (59 - 86 F).

Green-colored, oval shaped tablets embossed "EL510" on one side.

PLEASE REFER TO PACKAGE FOLDOUT FOR WARNINGS AND PRECAUTIONS.

Keep out of reach of children.

Manufactured for:

Elorac, Inc.

Vernon Hills, IL 60061

Rev. 07/15

140613